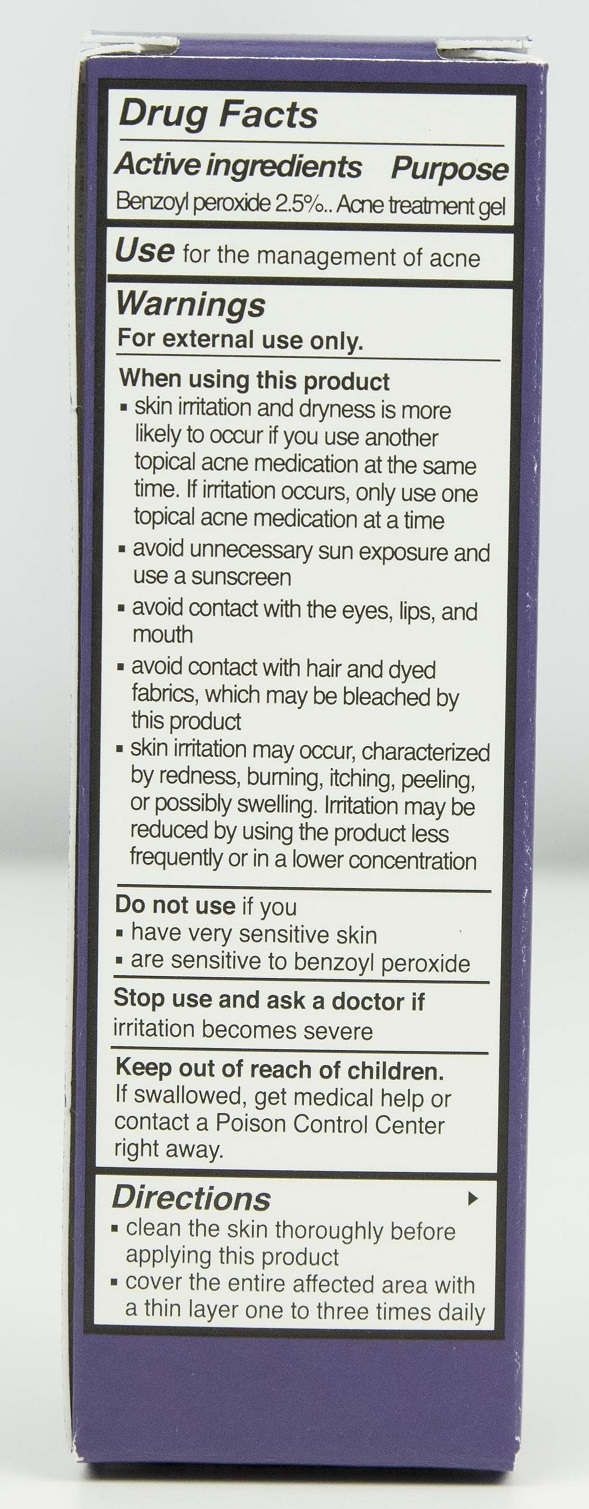 DRUG LABEL: SLMD AM Benzoyl Peroxide Acne Treatment
NDC: 59958-402 | Form: GEL
Manufacturer: Owen Biosciences, Inc.
Category: otc | Type: HUMAN OTC DRUG LABEL
Date: 20230116

ACTIVE INGREDIENTS: BENZOYL PEROXIDE 2.5 g/100 g
INACTIVE INGREDIENTS: WATER 70.14 g/100 g; DIMETHICONE 3.8 g/100 g; GLYCERYL STEARATE SE 2 g/100 g

SLMD AM Benzoyl Peroxide Acne Treatment

Active Ingredients

Benzoyl Peroxide 2.5%

Use

for the management of acne

Warnings For external use only

When using this product

skin irritation and dryness is more likely to occur if you use another topical acne medication at the same time. If irritation occurs, only use one topical acne medication at a time.

- avoid unnecessary sun exposure and use a sunscreen
- avoid contact with the eyes, lips and mouth
- avoid contact with hair and dyed fabrics, which may be bleached by this product
- skin irritation may occur, characterized by redness, burning, itching, peeling, or possibly swelling. Irritation may be reduced by using this product less frequently or in a lower concentration

Keep out of reach of children.

If swallowed, get medical help or contact a Poison Control Center right away.

Directions

- Clean the skin thoroughly before applying this product
- cover the entire affected area with a thin layer one to three times daily

PURPOSE

acne treatment

DOSAGE AND ADMINISTRATION

topical cleanser

Inactive ingredients

Water (Aqua)
Behenoxy Dimethicone
Cyclohexasiloxane
Cyclopentasiloxane
Dimethicone
Glyceryl Stearate SE
Acetyl Carboxymethyl Cocoyl-Glycine
Lysozyme
Phenoxyethanol
Tocopheryl Acetate
Decylene Glycol
Maltodextrin
Glyceryl Stearate
PEG-100 Stearate
Caprylyl Glycol
C13-14 Isoparaffin
Laureth-7
Polyacrylamide
Sodium Carboxymethyl Betaglucan
Cocoglycerides
Glycerin
Lecithin
Palmitoyl Myristyl Serinate
Syringa Vulgaris (Lilac) Extract
Butylene Glycol
Propanediol
Mirabilis Jalapa Extract
Aloe Barbadensis Leaf Juice
Capryloyl Glycine
Polyglyceryl-10 Laurate
Tromethamine
Beta-Glucan
Myristoyl Tetrapeptide-13
Acrylates/C10-30 Alkyl Acrylate Crosspolymer

Do not use if

- have very senstive skin
- are sensitive to benzoyl peroxide

Stop us and ask a doctor if

irritation becomes severe

Acne Lotion Back.jpg